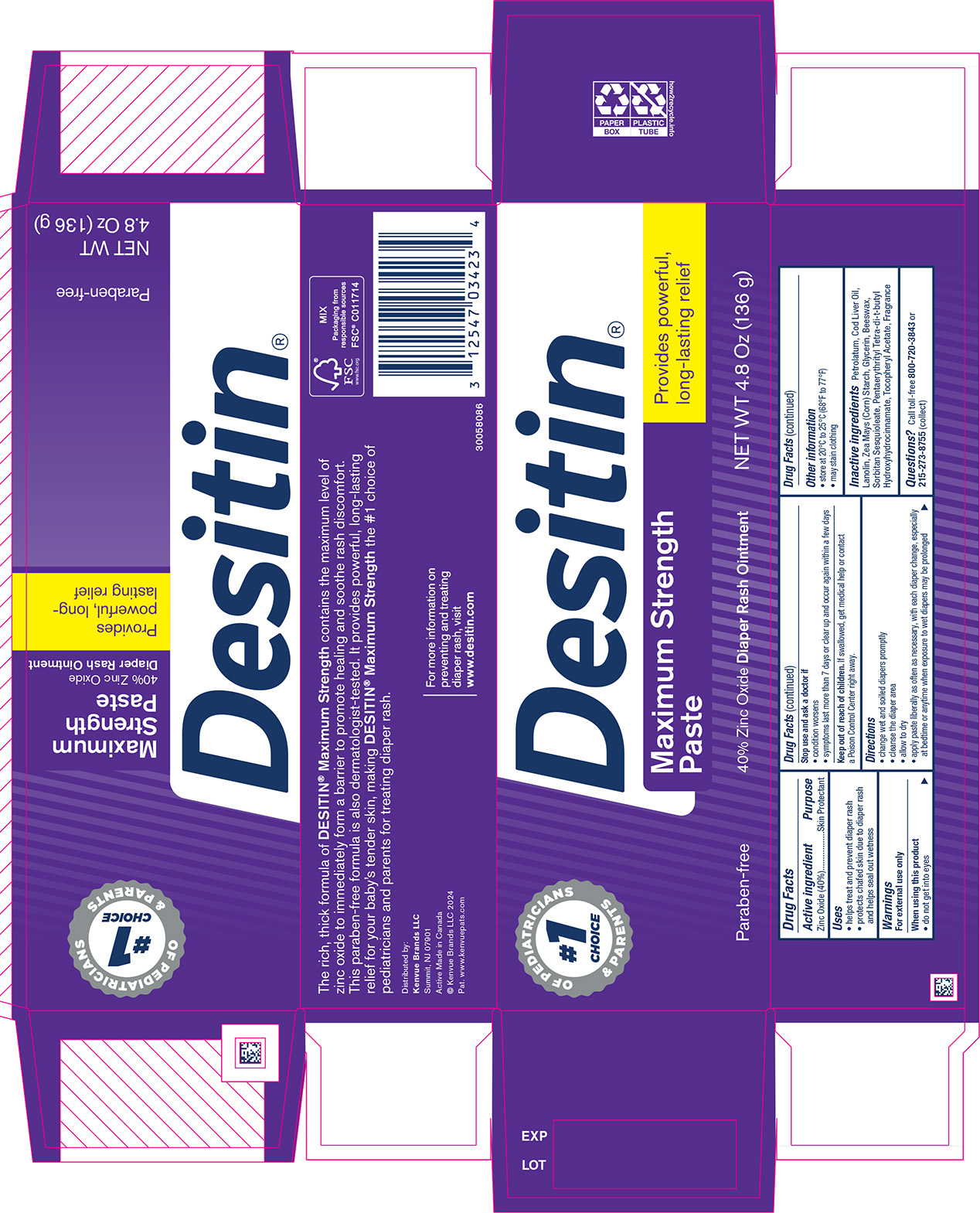 DRUG LABEL: Desitin Maximum Strength Zinc Oxide Diaper Rash
NDC: 69968-0848 | Form: PASTE
Manufacturer: Kenvue Brands LLC
Category: otc | Type: HUMAN OTC DRUG LABEL
Date: 20250228

ACTIVE INGREDIENTS: ZINC OXIDE 400 mg/1 g
INACTIVE INGREDIENTS: COD LIVER OIL; LANOLIN; PETROLATUM; STARCH, CORN; GLYCERIN; SORBITAN SESQUIOLEATE; YELLOW WAX; .ALPHA.-TOCOPHEROL ACETATE; PENTAERYTHRITOL TETRAKIS(3-(3,5-DI-TERT-BUTYL-4-HYDROXYPHENYL)PROPIONATE)

Desitin Maximum Strength Paste
40% Zinc Oxide Diaper Rash Ointment

Drug Facts

Active ingredient

Zinc Oxide (40%)

Purpose

Skin Protectant

Uses

• helps treat and prevent diaper rash

• protects chafed skin due to diaper rash and helps seal out wetness

Warnings

For external use only

When using this product

- do not get into eyes

Stop use and ask a doctor if

- condition worsens
- symptoms last more than 7 days or clear up and occur again within a few days

Keep out of reach of children. If swallowed, get medical help or contact a Poison Control Center right away.

Directions

• change wet and soiled diapers promptly

• cleanse the diaper area

• allow to dry

• apply paste liberally as often as necessary, with each diaper change, especially at bedtime or anytime when exposure to wet diapers may be prolonged

Other information

• store at 20°C to 25°C (68°F to 77°F)

• may stain clothing

Inactive ingredients

Petrolatum, Cod Liver Oil, Lanolin, Zea Mays (Corn) Starch, Glycerin, Beeswax, Sorbitan Sesquioleate, Pentaerythrityl Tetra-di-t-butyl Hydroxyhydrocinnamate, Tocopheryl Acetate, Fragrance

Questions?

Call toll-free 800-720-3843 or 215-273-8755 (collect)

Distributed by:

Kenvue Brands LLC
Summit, NJ 07901

PRINCIPAL DISPLAY PANEL - 136 g Tube in a Carton Label

#1 CHOICE OF PEDIATRICIANS

& PARENTS

Paraben-free

Desitin®

Maximum Strength Paste

40% Zinc Oxide Diaper Rash Ointment

Provides powerful,

long-lasting relief

NET WT 4.8 Oz (136 g)